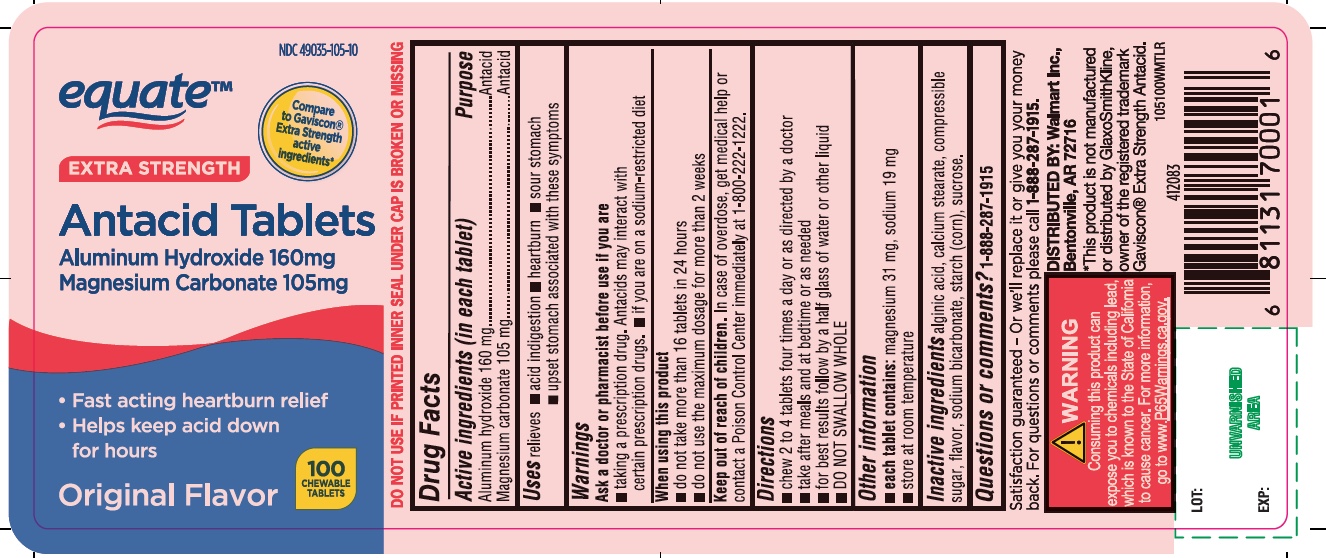 DRUG LABEL: equate Extra Strength Antacid
NDC: 49035-105 | Form: TABLET, CHEWABLE
Manufacturer: Wal-Mart Stores,Inc
Category: otc | Type: HUMAN OTC DRUG LABEL
Date: 20251027

ACTIVE INGREDIENTS: ALUMINUM HYDROXIDE 160 mg/1 1; MAGNESIUM CARBONATE 105 mg/1 1
INACTIVE INGREDIENTS: ALGINIC ACID; CALCIUM STEARATE; CORN SYRUP; SODIUM BICARBONATE; STARCH, CORN; SUCROSE

equate™ Extra Strength Antacid Chewable Tablets Original Flavor

Active ingredients (in each tablet)

Aluminum hydroxide 160 mg

Magnesium carbonate 105 mg

Purpose

Antacid

Antacid

Uses

relieves

- acid indigestion
- heartburn
- sour stomach
- upset stomach associated with these symptoms

Warnings

Ask a doctor or pharmacist before use if you are

- taking a prescription drug. Antacids may interact with certain prescription drugs.
- If you are on a sodium-restricted diet

When using this product

- do not take more than 16 tablets in 24 hours
- do not use the maximum dosage for more than 2 weeks

Keep out of reach of children.

In case of overdose, get medical help or contact a Poison Control Center immediately.1-800-222-1222

Directions

- chew 2 to 4 tablets four times a day or as directed by a doctor
- take after meals and at bedtime or as needed
- for best results follow by a half glass of water or other liquid
- DO NOT SWALLOW WHOLE

Other information

- e ach tablet contains:magnesium 31 mg, sodium 19 mg
- Store at room temperature

Inactive ingredients

alginic acid, calcium stearate, compressible sugar, flavor, sodium bicarbonate, starch (corn), sucrose.

Questions or comments?

1-888-287-1915

Principal Display Panel

NDC 49035-105-10

equate™

Compare to Gaviscon® Extra Strength Active Ingredients*

EXTRA STRENGTH

Antacid Tablets

Aluminum Hydroxide 160 mg,

Magnesium Carbonate 105 mg

- Fast-acting heartburn relief
- Helps keep acid down for hours

Original Flavor

100 CHEWABLE TABLETS

DO NOT USE IF PRINTED SEAL UNDER CAP IS TORN OR MISSING

Distributed by:

Wal-Mart Stores, Inc.,

Bentonville, AR 72716

Satisfaction guaranteed- Or we’ll replace it or give you your money back. For questions or comments please call 1-888-287-1915

*This product is not manufactured or distributed by GlaxoSmithKline, owner of the registered trademark Gaviscon® Extra Strength Antacid.